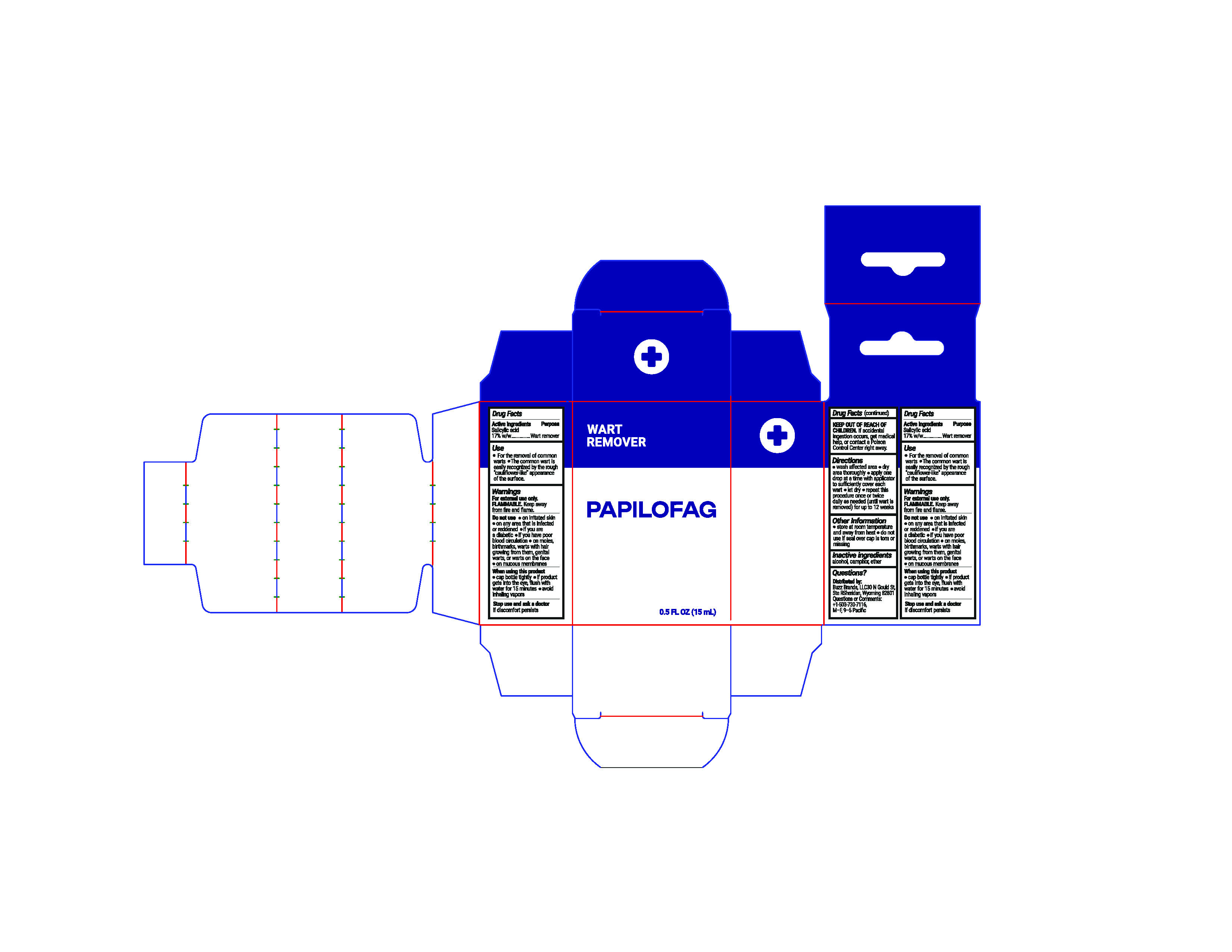 DRUG LABEL: Wart Remover
NDC: 10095-505 | Form: SOLUTION
Manufacturer: World Perfumes Inc
Category: otc | Type: HUMAN OTC DRUG LABEL
Date: 20250716

ACTIVE INGREDIENTS: SALICYLIC ACID 17 g/100 mL
INACTIVE INGREDIENTS: ALCOHOL; CAMPHOR (SYNTHETIC); ETHER

Papilofag 0.5oz

Drug Facts

Active ingredient: Salicylic acid 17% w/w

Purpose:

Wart Remover

Purpose

Purpose: Wart Remover

Warnings

For external use only.

FLAMMABLE. Keep away from fire and flame.

Do not use:

On irritated skin

On any area that is infected or reddened

If you are diabetic

If you have poor blood circulation

On moles, birthmarks, warts with hair growing from them, genital warts, or warts on the face or on mucous membranes

Do not use

On irritated skin

On any area that is infected or reddened

If you are diabetic

If you have poor blood circulation

On moles, birthmarks, warts with hair growing from them, genital warts, or warts on the face or on mucous membranes

When using this product

Cap bottle tightly

If product gets into eyes, flush with water for 15 minutes

Avoid inhaling vapors

Stop use and ask a doctor if discomfort persists

Stop Use

Stop use and ask a doctor if discomfort persists

Keep out of reach of children. If swallowed, get medical help or contact a Poison Control Center right away.

Directions

· • Wash affected area

· • Dry area thoroughly

· • Apply one drop at a time with applicator to sufficiently cover each wart

· • Let dry

· • Repeat this procedure once or twice daily as needed (until wart is removed) for up to 12 weeks

Other Information

· Store at room temperature away from heat

· • Do not use if seal over cap is torn or missing

Inactive Ingredients

Alcohol, Camphor, ether

Dosage

Wash affected area

Dry area thoroughly

Apply one drop at a time with applicator to sufficiently cover each wart

Let dry

Repeat this procedure once or twice daily as needed (until wart is removed) for up to 12 weeks

QUESTIONS

Buzz Brands LLC

30 N Gould St Suite R Sheridan, Wyoming 829801

Questions or Comments

+1-503-730-7116

M-F, 9-5 Pacific

Title

Papilofag

Wart Remover

0.5 fl pz (15mL)